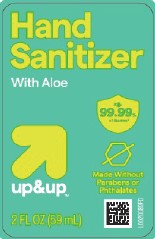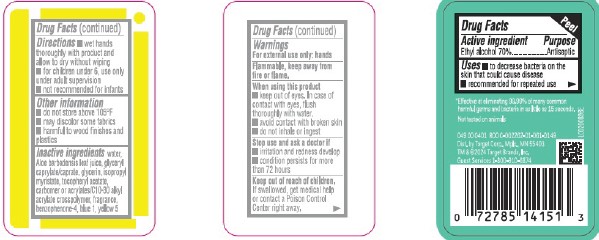 DRUG LABEL: Advanced Hand Sanitizer
NDC: 11673-439 | Form: GEL
Manufacturer: Target Corporation
Category: otc | Type: HUMAN OTC DRUG LABEL
Date: 20260218

ACTIVE INGREDIENTS: ALCOHOL 70 mL/100 mL
INACTIVE INGREDIENTS: WATER; ALOE VERA LEAF; GLYCERYL CAPRYLATE/CAPRATE; GLYCERIN; ISOPROPYL MYRISTATE; .ALPHA.-TOCOPHEROL ACETATE; CARBOMER HOMOPOLYMER, UNSPECIFIED TYPE; CARBOMER INTERPOLYMER TYPE A (ALLYL SUCROSE CROSSLINKED); SULISOBENZONE; FD&C BLUE NO. 1; FD&C YELLOW NO. 5

Up & Up 439.001/439AB-AC rev 1
Advanced Hand Sanitizer with Aloe

Active ingredient

Ethyl alcohol 70%

Purpose

Antiseptic

Uses

- to decrease bacteria on the skin that could cause disease
- recommended for repeated use

Warnings

For external use only: hands

Flammable, keep away from heat or flame.

When using this product

- keep out of eyes. In case of contact with eyes, flush thoroughly with water.
- avoid contact with broken skin
- do not inhale or ingest

Stop use and ask a doctor if

- irritation and redness develop
- condition persists for more than 72 hours

Keep out of reach of children.

If swallowed, get medical help or contact a Poison Control Center right away.

Directions

- wet hands thoroughly with product and allow to dry without wiping
- for children under 6, use only under adult supervision
- not recommended for infants

Other information

- do not store above 105F
- may discolor some fabrics
- harmful to wood finishes and plastics

Inactive ingredients

water, aloe barbadensis leaf juice, glyceryl caprylate/caprate, glycerin, isopropyl myristate, tocopheryl acetate, acrylates/C10-30 alkyl acrylate crosspolymer, fragrance, benzophenone-4, blue 1, yellow 5

Claims

*Effective at eliminating more than 99.99% of many common harmful germs and bacteria in as little as 15 seconds.

Not tested on animals

Adverse reaction

049 00 0401 R00 C-002262-01-61-0149

Dist. by Target Corp. Mpls., MN 55403

TM & ©2024 Target Brands, Inc.

Guest Services 1-800-910-6874

Principal display panel

Hand Sanitizer

With Aloe

Kills 99.99% of germs*

up + up™

Made Without Parabens or Phithalates

2 FL OZ (59 mL)